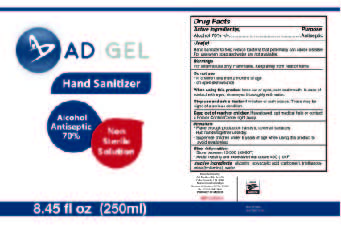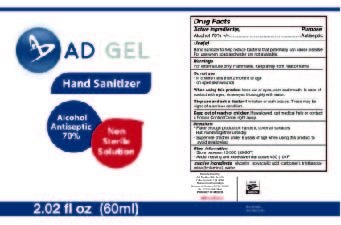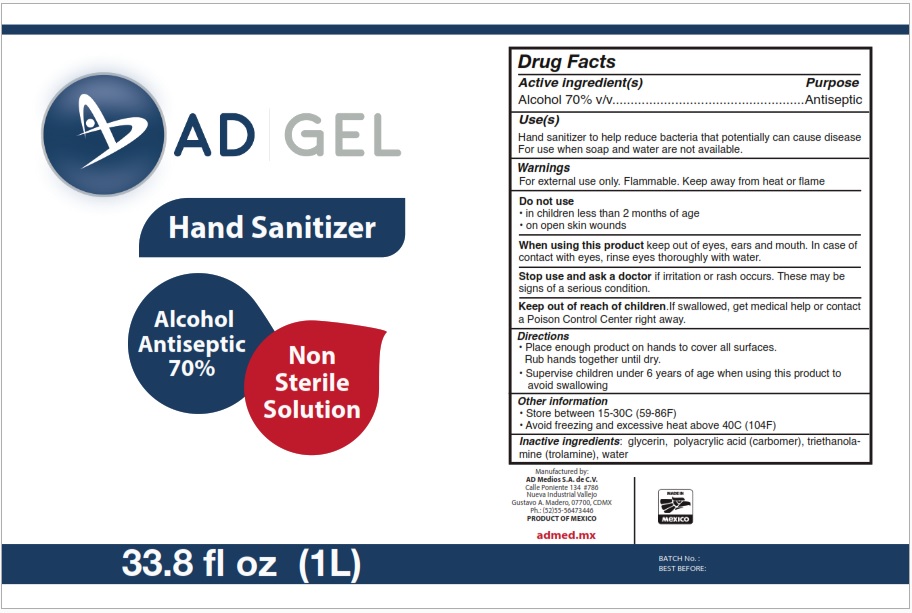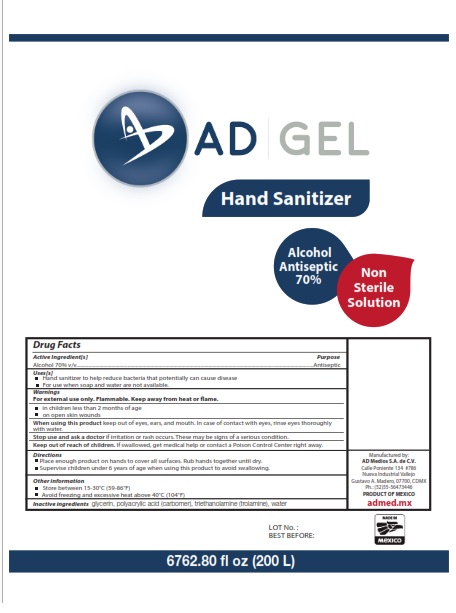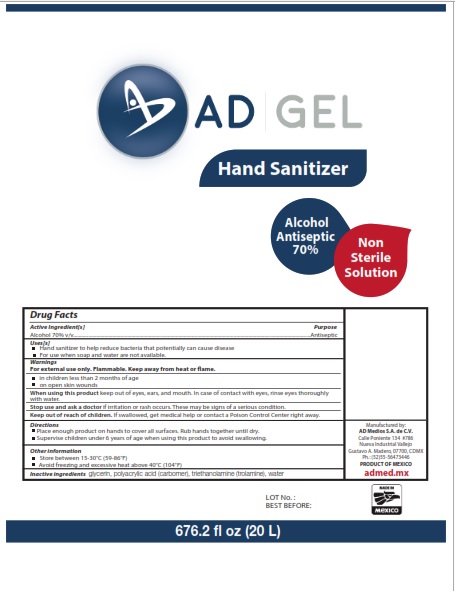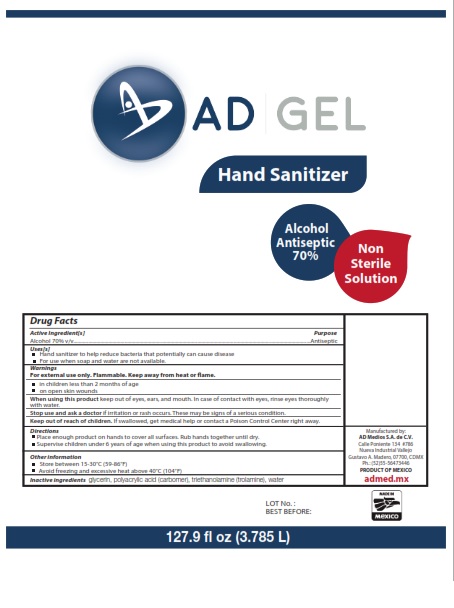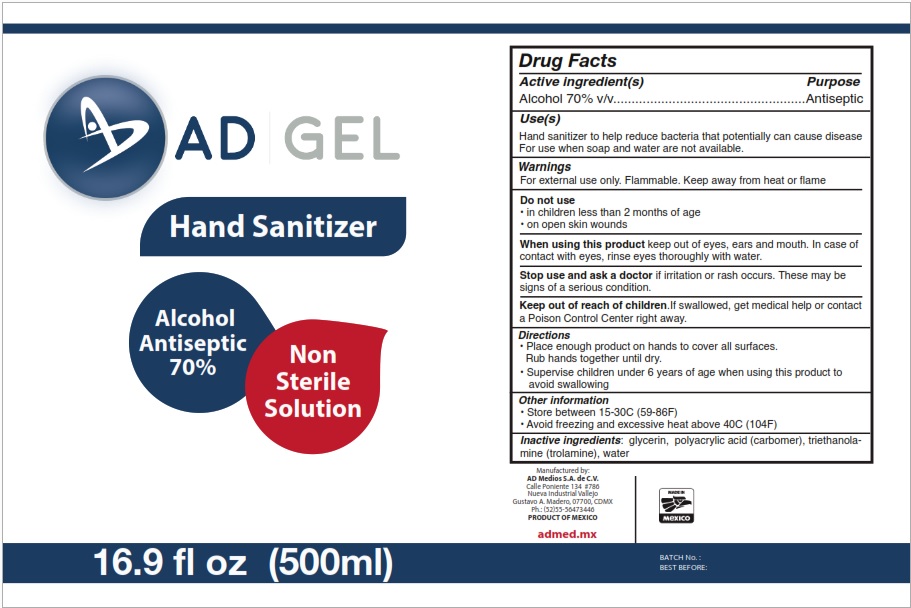 DRUG LABEL: Ad Gel
NDC: 77739-002 | Form: GEL
Manufacturer: AD MEDIOS, S.A. de C.V.
Category: otc | Type: HUMAN OTC DRUG LABEL
Date: 20201208

ACTIVE INGREDIENTS: ALCOHOL 70 mL/100 mL
INACTIVE INGREDIENTS: POLYACRYLIC ACID (8000 MW) 0.35 mL/100 mL; GLYCERIN 1.5 mL/100 mL; TROLAMINE 0.25 mL/100 mL; WATER 27.9 mL/100 mL

Active Ingredient(s)

Alcohol 70% v/v. Purpose: Antiseptic

Purpose

Antiseptic, Hand Sanitizer

Use

Hand Sanitizer to help reduce bacteria that potentially can cause disease. For use when soap and water are not available.

Warnings

For external use only. Flammable. Keep away from heat or flame

Do not use

- in children less than 2 months of age
- on open skin wounds

When using this product keep out of eyes, ears, and mouth. In case of contact with eyes, rinse eyes thoroughly with water.
Stop use and ask a doctor if irritation or rash occurs. These may be signs of a serious condition.
Keep out of reach of children. If swallowed, get medical help or contact a Poison Control Center right away.

Stop use and ask a doctor if irritation or rash occurs. These may be signs of a serious condition.

Keep out of reach of children. If swallowed, get medical help or contact a Poison Control Center right away.

Directions

- Place enough product on hands to cover all surfaces. Rub hands together until dry.
- Supervise children under 6 years of age when using this product to avoid swallowing.

Other information

- Store between 15-30C (59-86F)
- Avoid freezing and excessive heat above 40C (104F)

Inactive ingredients

glycerin, polyacrylic acid (Carbomer), triethanolamine (trolamine), Water.

Package Label - Principal Display Panel

500 mL NDC: 77739-002-01

PACKAGE LABEL

1000 mL NDC: 77739-002-02

PACKAGE LABEL

3785 mL NDC: 77739-002-03

PACKAGE LABEL

20000 mL NDC: 77739-002-04

PACKAGE LABEL

200000 mL NDC: 77739-002-05

PACKAGE LABEL

60 mL NDC: 77739-002-07

PACKAGE LABEL

250 mL NDC: 77739-002-06